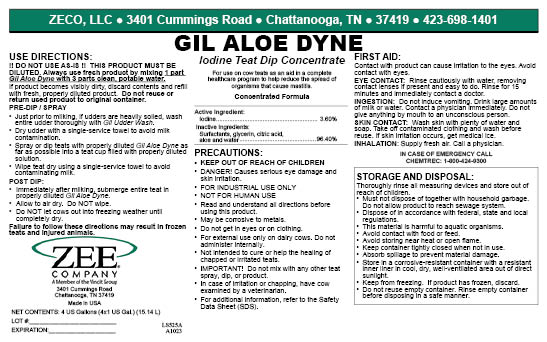 DRUG LABEL: Gil Aloe Dyne
NDC: 86161-008 | Form: CONCENTRATE
Manufacturer: ZECO, LLC
Category: animal | Type: OTC ANIMAL DRUG LABEL
Date: 20240126

ACTIVE INGREDIENTS: iodine 36 g/1 L
INACTIVE INGREDIENTS: C12-16 PARETH-5; SODIUM HYDROXIDE; ANHYDROUS CITRIC ACID; GLYCERIN; ALOE VERA LEAF; ISOPROPYL ALCOHOL

Gil Aloe Dyne

PURPOSE

Iodine Teat Dip ConcentrateFor use on cow teats as an aid in a complete healthcare program to help reduce the spread of organisms that cause mastitis.

Acive Ingredient:

Iodine ........................................................3.60%

PRECAUTIONS:

- KEEP OUT OF REACH OF CHILDREN
- DANGER! Causes serious eye damage and skin irritation.
- FOR INDUSTRIAL USE ONLY
- NOT FOR HUMAN USE
- Read and understand all directions before using this product.
- May be corrosive to metals.
- Do not get in eyes or on clothing.
- For external use only on dairy cows. Do not administer internally.
- Not intended to cure or help the healing of chapped or irritated teats.
- IMPORTANT: Do not mix with any other teat spray, dip, or product.
- In case of irritation or chapping, have cow examined by a veterinarian.
- For additional information refer to the Safety Data Sheet (SDS).

DOSAGE AND ADMINISTRATION

USE DIRECTIONS:

!! DO NOT USE AS-IS !! THIS PRODUCT MUST BE DILUTED. Always use fresh product by mixing 1 part Gil Aloe Dyne with 3 parts clean, potable water.

If product becomes visibly dirty, discard contents and refill with fresh, properly diluted product.

Do not reuse or return used product to original container.

PRE-DIP / SPRAY

- Just prior to milking, if udders and teats are heavily soiled, wash entire udder thoroughly with Gil Udder Wash.
- Dry udder with a single-service towel to avoid milk contamination.
- Spray or dip teats with properly diluted Gil Aloe Dyne as far as possible into a teat cup filled with properly diluted solution.
- Wipe teat dry using a single-service towel to avoid contaminating milk.

POST DIP:

- Immediately after milking, submerge entire teat in properly diluted Gil Aloe Dyne.
- Allow to air dry. Do NOT wipe.
- Do NOT let cows out into freezing weather until completely dry.

Failure to follow these directions may result in frozen teats and injured animals.

PACKAGE LABEL

Add image transcription here...